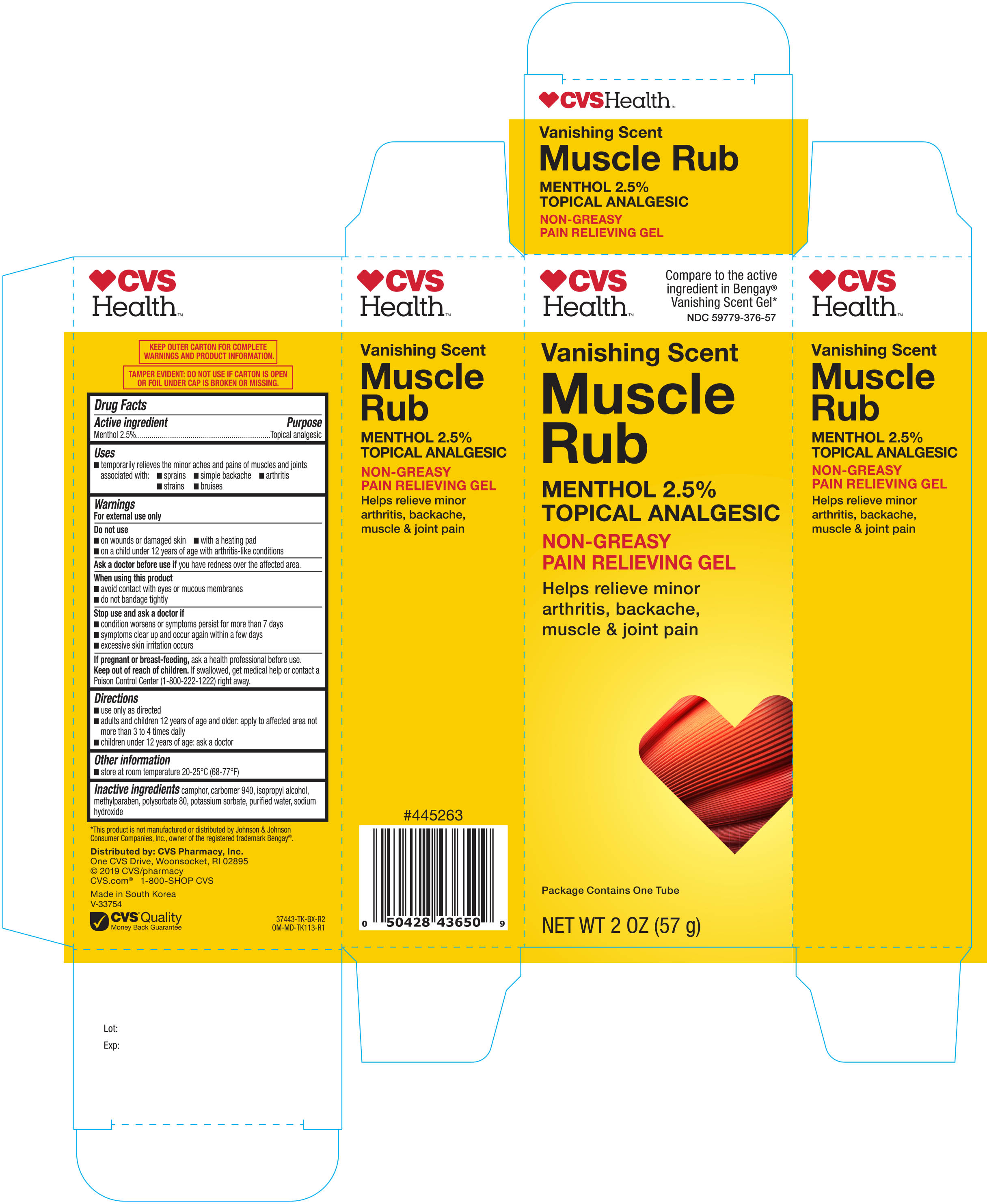 DRUG LABEL: CVS VANISHING SCENT MUSCLE RUB
NDC: 59779-376 | Form: GEL
Manufacturer: CVS PHARMACY
Category: otc | Type: HUMAN OTC DRUG LABEL
Date: 20190315

ACTIVE INGREDIENTS: MENTHOL 2.5 g/100 g
INACTIVE INGREDIENTS: POTASSIUM SORBATE; POLYSORBATE 80; SODIUM HYDROXIDE; ISOPROPYL ALCOHOL; CAMPHOR (SYNTHETIC); METHYLPARABEN; WATER; CARBOMER HOMOPOLYMER TYPE C

CVS Vanishing Scent Muscle Rub Pain Relieving Gel 2oz (37443, 2019)

Active ingredient Purpose

Menthol 2.5%..................................................................................Topical Analgesic

Uses

temporarily relieves the minor aches and pains of muscles and joints associated with:

- sprains
- simple backache
- arthritis
- strains
- bruises

Warnings

For external use only

Do not use

- on wounds or damaged skin
- with a heating pad
- on a child under 12 years of age with arthritis-like conditions

Ask a doctor before use if you have redness over the affected area

When using this product

- avoid contact with eyes or mucous membranes
- do not bandage tightly

Stop use and ask a doctor if

- conditions worsens or symptoms persist for more than 7 days
- symptoms clear up and occur again within a few days
- excessive skin irritation occurs

Keep out of reach of children. If swallowed, get medical help or contact a Poison Control Center immediately.

PREGNANCY OR BREAST FEEDING

If pregnant, or breast-feeding, ask a health professional before use.

Directions

- adults and children 12 years of age and older: apply to affected area not more than 3 to 4 times daily
- children under 12 years of age : ask a doctor

Other information

- Store between 20-25oC (68-77oF)

Inactive ingredients

camphor, carbomer 940, isopropyl alcohol, mehtylparaben, polysorbate 80, potassium sorbate, purified water, sodium hydroxide

DOSAGE AND ADMINISTRATION

Distributed by:

CVS Pharmacy, Inc.

One CVS Drive, Woonsocket, RI 02895

www.cvs.com 1-800-SHOP CVS

Made in South Korea